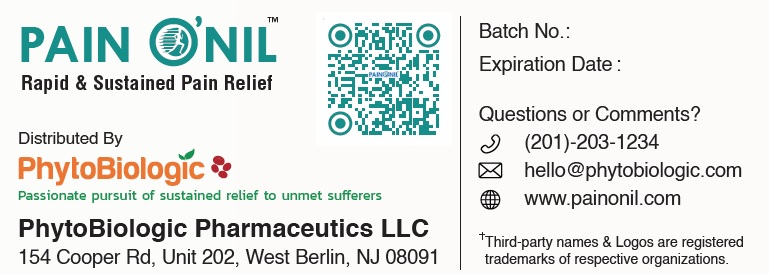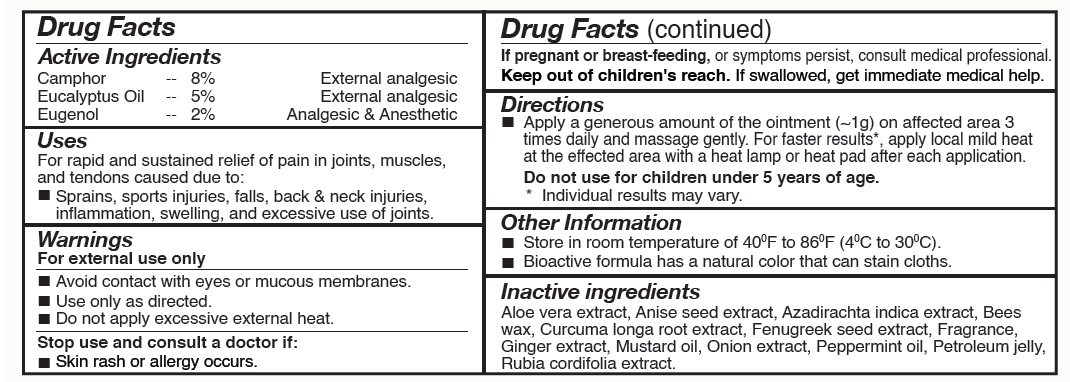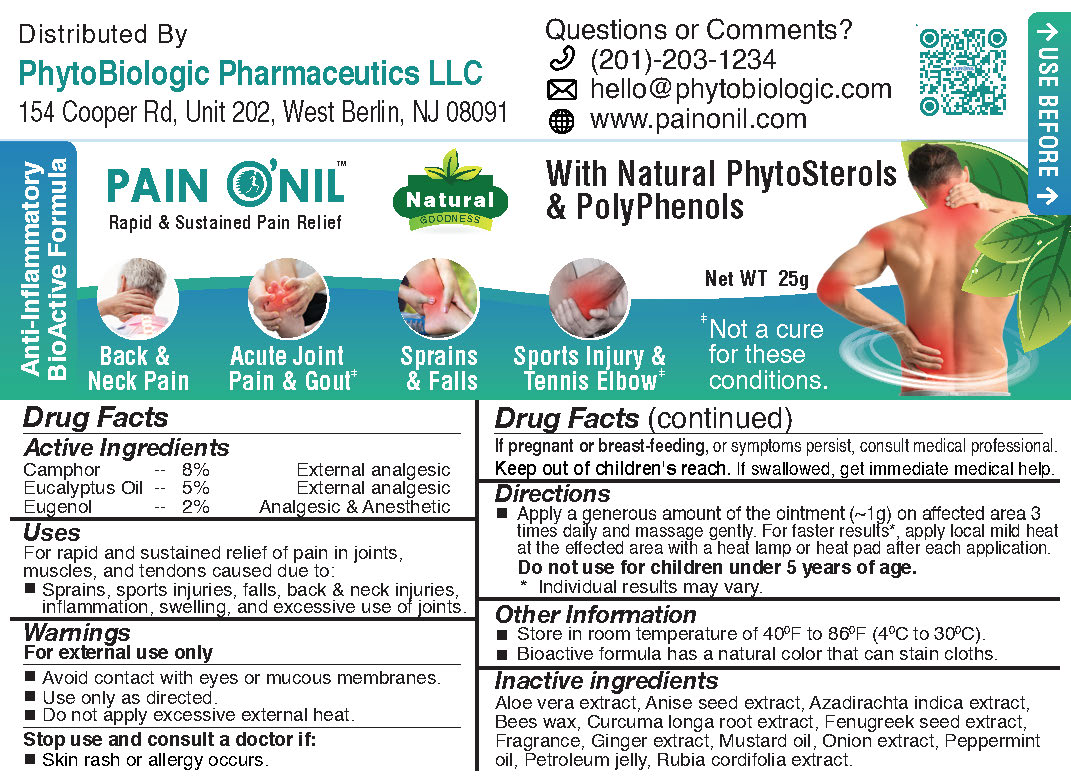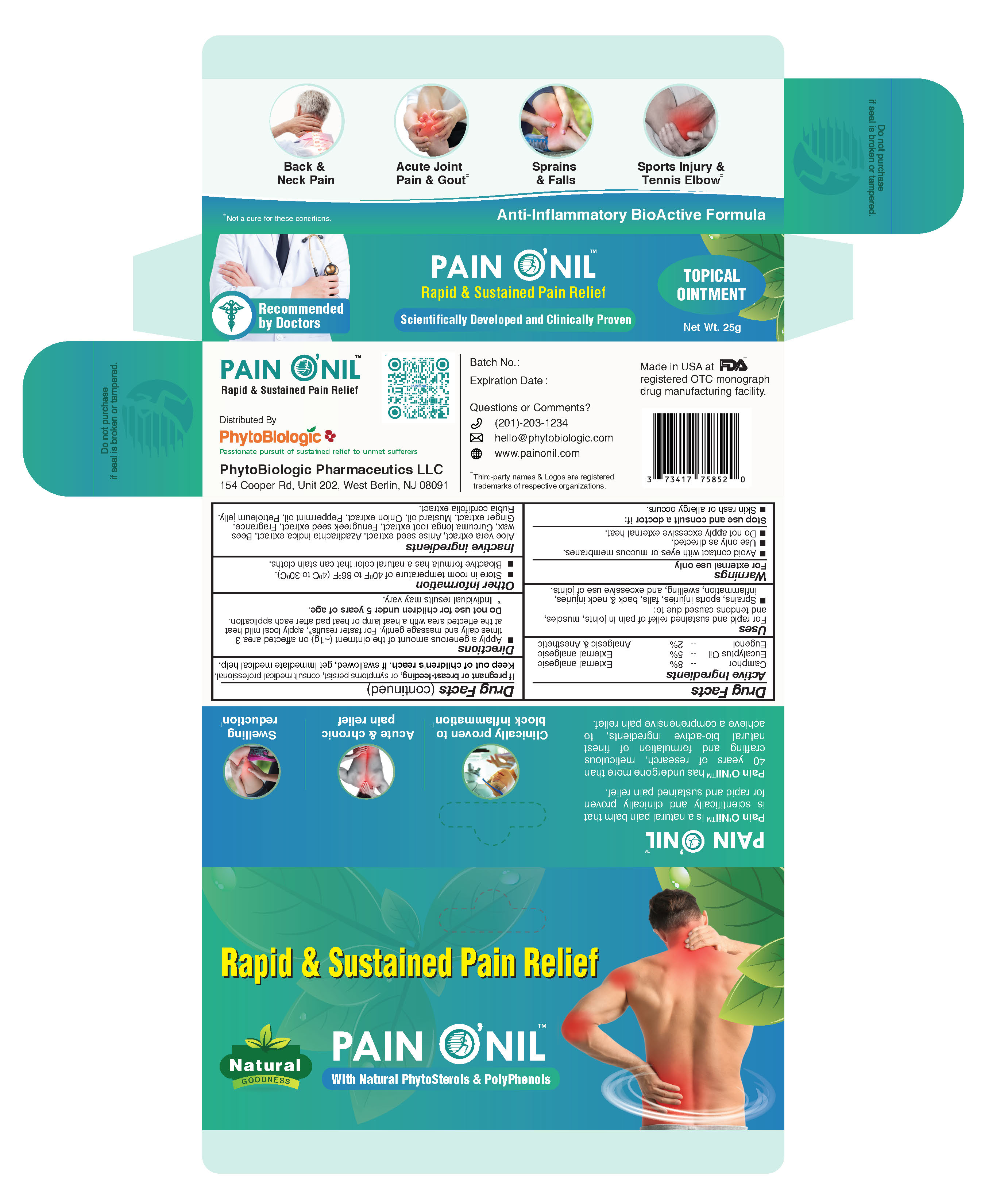 DRUG LABEL: PainONil
NDC: 73417-758 | Form: OINTMENT
Manufacturer: PhytoBiologic Pharmaceutics LLC
Category: otc | Type: HUMAN OTC DRUG LABEL
Date: 20210724

ACTIVE INGREDIENTS: CAMPHOR (NATURAL) 80 mg/1 g; EUGENOL 20 mg/1 g; EUCALYPTUS OIL 50 mg/1 g
INACTIVE INGREDIENTS: FENUGREEK SEED; MUSTARD OIL; PETROLATUM; PEPPERMINT OIL; AZADIRACHTA INDICA LEAF; YELLOW WAX; RUBIA CORDIFOLIA ROOT; ALOE VERA LEAF; TURMERIC; ONION JUICE; GINGER; ANISE OIL

PainONil 25g Tube for Sustained and Rapid Pain Relief

PainONil Active Ingredients

Active Ingredient | Strength | Purpose
Camphor | 8% | External analgesic
Eucalyptus oil | 5% | External analgesic
Eugenol | 2% | Analgesic & Anesthetic

Purpose

For rapid and sustained relief of pain.

Uses

For rapid and sustained relief of pain in joints, muscles, and tendons caused due to:

- Sprains
- sports injuries
- falls
- back & neck injuries
- inﬂammation
- swelling
- excessive use of joints

Warnings

- For external use only.
- Avoid contact with eyes and mucous membranes.
- Use only as directed.
- Stop use and consult a doctor if: Skin rash or allergy occurs.
- If pregnant or breast-feeding, or symptoms persist, consult medical professional.
- Keep out of children's reach. If swallowed, get immediate medical help.

Directions

Apply a generous amount of the ointment (~1g) on the affected area 3 times daily and massage gently. For faster results*, apply mild heat at the effected area with a heat lamp or heat pad after each application.

Do not use for children under 5 years of age.

* Individual results may vary.

When Using This Product

- Do not apply excessive external heat

Stop Use Section

Stop use of this product and consult a doctor If:

- Skin rash occurs

If pregnant or breat feeding

If pregnant or breast-feeding, or symptoms persist, consult medical professional before use

Keep Out of Reach of Children

Keep out of children's reach. If swallowed, get immediate medical help.

Other Information

- Store in room temperature 40^0F to 86^0F (4^0C to 30^0C)
- Bioactive formula has a natural color that can stain cloths

Inactive Ingredients

Aloe vera extract, Anise seed extract, Azadirachta indica extract, Beeswax, Curcuma longa root extract, Fenugreek seed extract, Fragrance, Ginger extract, Mustard oil, Onion extract, Peppermint oil, Petroleum jelly, Rubia cordifolia extract.

RECENT MAJOR CHANGES

- Active Ingredients (Camphor -- 8% External analgesic, Eucalyptus Oil -- 5% External analgesic, Eugenol -- 2% Analgesic & Anesthetic)
- Inactive ingredients
  Aloe vera extract, Anise seed extract, Azadirachta indica extract, Beeswax, Curcuma longa root extract, Fenugreek seed extract, Fragrance, Ginger extract, Mustard oil, Onion extract, Peppermint oil, Petroleum jelly, Rubia cordifolia extract.

Principal Display Panel - 25 g Tube & Carton

PainONilTM - 25 g Tube & Carton
NDC 73417-718-25

Net Wt: 0.90 OZ (25g)